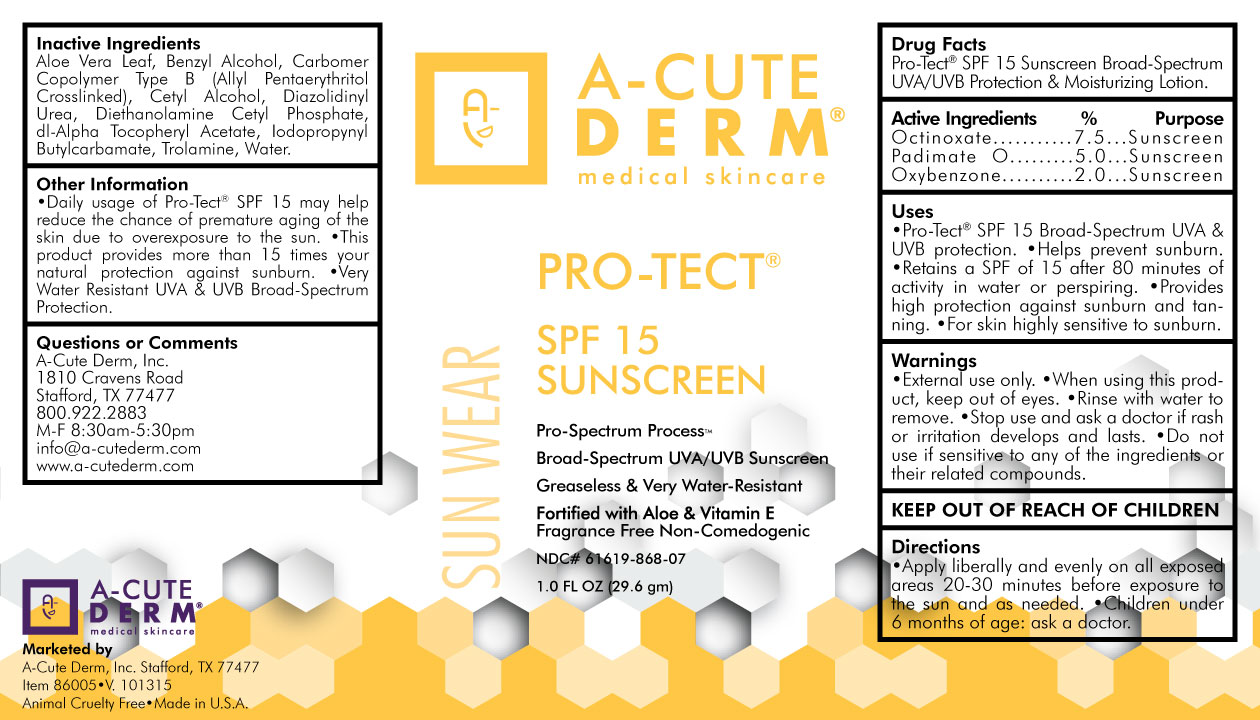 DRUG LABEL: PRO-TECT EVERYDAY SUNSCREEN SPF 15
NDC: 61619-868 | Form: LOTION
Manufacturer: A-Cute Derm, Incorporated
Category: otc | Type: HUMAN OTC DRUG LABEL
Date: 20160504

ACTIVE INGREDIENTS: OCTINOXATE 75 mg/1 g; OXYBENZONE 20 mg/1 g; PADIMATE O 50 mg/1 g
INACTIVE INGREDIENTS: ALOE VERA LEAF; BENZYL ALCOHOL; CARBOMER COPOLYMER TYPE B (ALLYL PENTAERYTHRITOL CROSSLINKED); CETYL ALCOHOL; DIAZOLIDINYL UREA; DIETHANOLAMINE CETYL PHOSPHATE; .ALPHA.-TOCOPHEROL ACETATE, DL-; IODOPROPYNYL BUTYLCARBAMATE; TROLAMINE; WATER

DRUG FACTS

Pro-Tect® SPF 15+ Sunscreen Broad-Spectrum UVA/UVB Protection & Moisturizing Lotion

Active Ingredients

Octinoxate...........................................................7.5%

Oxybenzone.........................................................2.0%

Padimate O...........................................................5.0%

Purpose

Sunscreen

Uses

•Pro-Tect® SPF 15+ Broad-Spectrum UVA & UVB protection. •Helps prevent sunburn. •Retains a SPF

of 15+ after 80 minutes of activity in water of perspiring. •Provides high protection against sunburn and

tanning. •For skin highly sensitive to sunburn.

Warnings

•External use only. •When using this product, keep out of eyes. •Rinse with water to remove. •Stop use and ask a doctor if rash or irritation develops and lasts. •Do not use if sensitive to any of the ingredients of their related compounds.

Directions

•Apply liberally and evenly on all exposed areas 20-30 minutes before exposure to the sun and as needed.

•Children under 6 months of age: ask a doctor.

Inactive ingredients

Aloe Vera Leaf, Benzyl Alcohol, Carbomer Copolymer Type B (Allyl Pentaerythritol Crosslinked),

Cetyl Alcohol, Diazolidinyl Urea, Diethanolamine Cetyl Phospate, dl-Alpha Tocopheryl Acetate,

Iodopropynyl Butylcarbamate, Trolamine, Water.

Other Information

•Daily usage of Pro-Tect SPF15+ may help reduce the chance of premature aging of the skin due to

overexposure to the sun. •This product provides more than 15 times your natural protection against

sunburn. •Very Water Resistant UVA & UVB Broad-Spectrum Protection. •This product may stain light

colored fabrics if washed with bleach. Wash clothing without bleach to remove safely.

Questions or Comments

Bio-Medical & Pharm. Mfg. Corp.

4311 South Dr.

Houston, TX 77053-4820

281-835-8051

M-F 8AM-5PM

www.bio-medicalmanufacturing.com

Principal Display Panel

Pro-Tect

SPF 15

Sunscreen

29.6 grams

NDC:61619-868-07